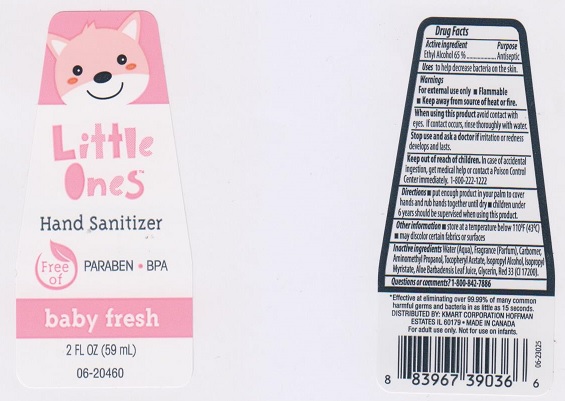 DRUG LABEL: Little Ones
NDC: 49738-413 | Form: LIQUID
Manufacturer: Kmart Corporation
Category: otc | Type: HUMAN OTC DRUG LABEL
Date: 20170523

ACTIVE INGREDIENTS: ALCOHOL 650 mg/1 mL
INACTIVE INGREDIENTS: WATER; CARBOMER 934; AMINOMETHYLPROPANOL; .ALPHA.-TOCOPHEROL ACETATE, DL-; ISOPROPYL ALCOHOL; ISOPROPYL MYRISTATE; ALOE VERA LEAF; glycerin; D&C RED NO. 33

Drug Facts

Active ingredient

Ethyl Alcohol 65%

Purpose

Antiseptic

Uses

to help decrease bacteria on the skin.

Warnings

For external use only.

- Flammable
- Keep away from source of heat or fire.

When using this product

avoid contact with eyes. If contact occurs, rinse thoroughly with water.

Stop use and ask a doctor if

irritation or redness develops and lasts.

Keep out of reach of children.

In case of accidental ingestion, get medical help or contact a Poison Control Center immediately. 1-800-222-1222

Directons

- put enough product in your palm to cover hands and rub hands together until dry
- children under 6 years should be supervised when using this product.

Other information

- store at a temperature below 110°F (43°C)
- may discolor certain fabrics or surfaces

Inactive ingredients

Water (Aqua), Fragrance (Parfum), Carbomer, Aminomethyl Propanol, Tocopheryl Acetate, Isopropyl Alcohol, Isopropyl Myristate, Aloe Barbadensis Leaf Juice, Glycerin, Red 33 (CI 17200).

Questions or comments?

1-800-842-7886